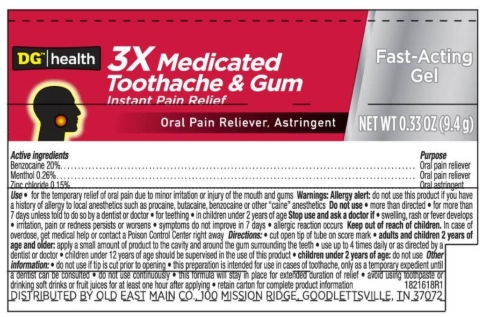 DRUG LABEL: DG 3x Medicated Toothache adn Gum Gel
NDC: 55910-816 | Form: GEL
Manufacturer: Dollar General
Category: otc | Type: HUMAN OTC DRUG LABEL
Date: 20251114

ACTIVE INGREDIENTS: BENZOCAINE 20 g/100 g; ZINC CHLORIDE 0.15 g/100 g; MENTHOL, UNSPECIFIED FORM 0.26 g/100 g
INACTIVE INGREDIENTS: POLYETHYLENE GLYCOL 3350; POLYETHYLENE GLYCOL 400; SACCHARIN SODIUM; SORBIC ACID; AMMONIUM GLYCYRRHIZATE

5820618 DG 3x Med Gel

ACTIVE INGREDIENT

Benzocaine 20%

Menthol 0.26%

Zinc chloride 0.15%

PURPOSE

Oral pain reliever

Oral pain reliever

Oral astringent

INDICATIONS AND USAGE

for the temporary relief of oral pain due to minor irritation or injury of the mouth and gums

Allergy alert: do not use this product if you have a history of allergy to local anesthetics such as procaine, butacaine, benzocaine or other "caine" anesthetics

Do not use * more than directed * for more than 7 days uness told to do so by a dentist or doctor * for teething * in children under 2 years of age

Stop use and ask a doctor if * swelling, rash or fever develops * irritation, pain or redness persists or worsens * symptoms do not improve in 7 days * allergeic reaction occurs

Keep out of reach of children. In case of overdose, get medical help or contact a Poison Control Center right away

DOSAGE AND ADMINISTRATION

cut open tip of tube on score mark * adults and children 2 years of age and older: apply a small amount of product to teh cavity and around the gum surrounding the teeth * use up to 4 times daily or as directed by a dentist or doctor * children under 12 years of age should be supervised in the use of this product * children under 2 years of age: do not use

do not use if tip is cut prior to opening * this preparation is intended for use in cases of toothache, only as a temporary expedient until a dentist can be consulted * do not use continuously * this formula will stay in place for extended duration of relief * avoid using toothpaste or drinking soft drinks or fruit juices for at least one hour after applying * retain carton for complete product information

INACTIVE INGREDIENT

ammonium glycyrrhizate, flavor, PEG-8, PEG-75, sodium saccharin, sorbic acid